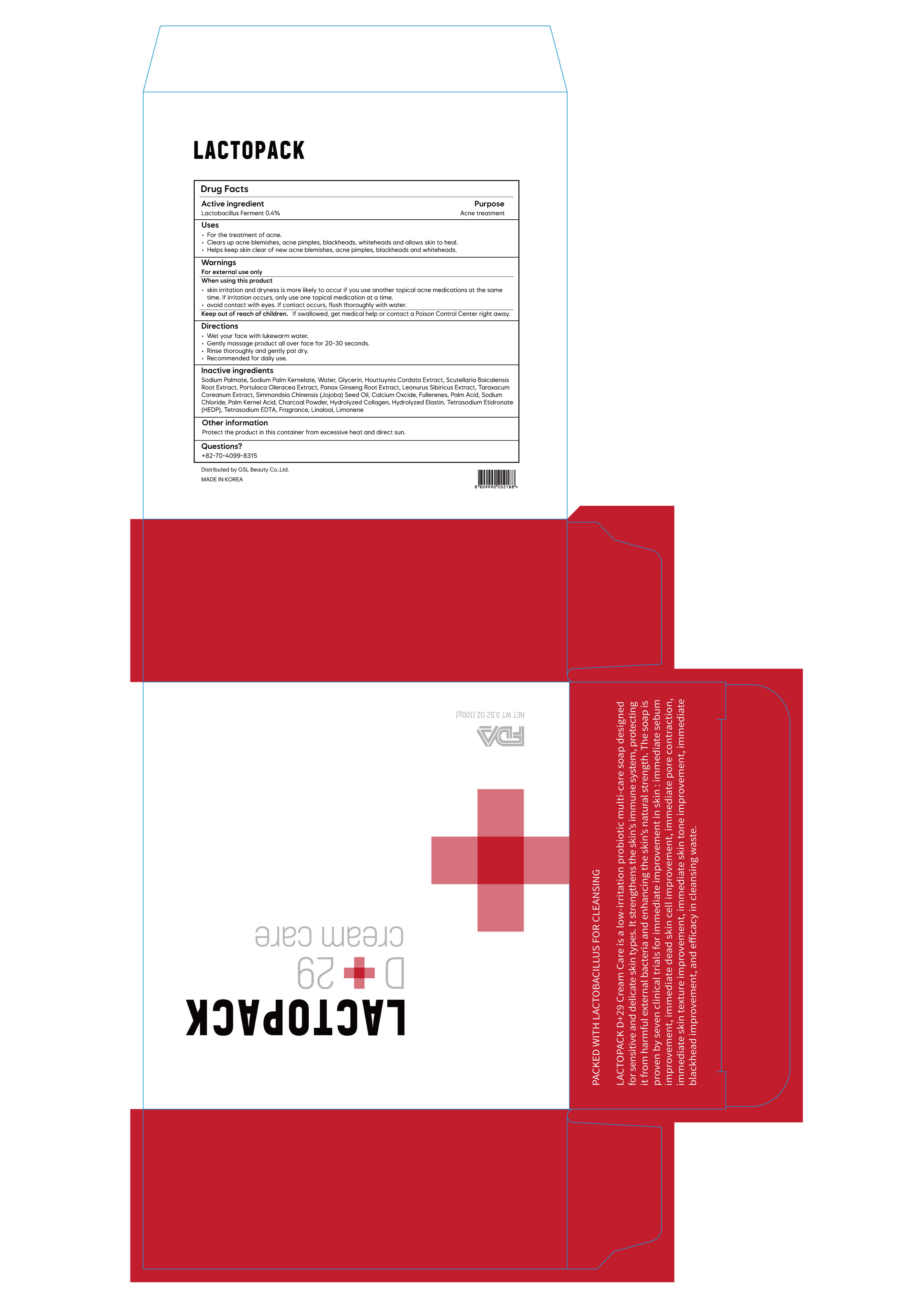 DRUG LABEL: Lacto Pack D29 Cream Care
NDC: 84419-302 | Form: SOAP
Manufacturer: GSL Beauty Co., Ltd
Category: otc | Type: HUMAN OTC DRUG LABEL
Date: 20240617

ACTIVE INGREDIENTS: LIMOSILACTOBACILLUS FERMENTUM 0.4 g/100 g
INACTIVE INGREDIENTS: SODIUM CHLORIDE; PALM KERNEL ACID; JOJOBA OIL; EDETATE SODIUM; PURSLANE; SODIUM PALM KERNELATE; WATER; BUCKMINSTERFULLERENE; SODIUM PALMATE; ACTIVATED CHARCOAL; HOUTTUYNIA CORDATA FLOWERING TOP; GLYCERIN; SCUTELLARIA BAICALENSIS ROOT; LINALOOL, (+/-)-; ETIDRONATE TETRASODIUM; LIMONENE, (+/-)-; LIME (CALCIUM OXIDE); HYDROLYZED BOVINE ELASTIN (BASE; 1000 MW); PALM ACID; ASIAN GINSENG

84419-302 Lacto Pack D29 Cream Care

Active ingredient

Lactobacillus Ferment 0.4%

Purpose

Acne, Anti-inflammatory

Use

It helps to treatment of atopic dermatitis

It helps to acne treatment

It helps to skin's refreshing and sedation
Antibacterial, Anti-inflammatory

Warning

Store in a cool and dry place.

Keep out of reach of children and pets.

Stop use and ask a doctor if

irritation and redness develops.

Direction

Use daily on face, body and hair as well, for even better effectiveness of removing make up and wastes in pores. Especially secondary cleansing has an effect in washing and tone up.

Inactive ingredients

Sodium Palmate, Sodium Palm Kernelate, Glycerin, Houttuynia Cordata Extract, Water, Scutellaria Baicalensis Root Extract, Portulaca Oleracea Extract, Panax Ginseng Root Extract, Leonurus Sibiricus Extract, Taraxacum Coreanum Extract,
Simmondsia Chinensis (Jojoba) Seed Oil, Calcium Oxcide, Fullerenes, Charcoal Powder, Hydrolyzed Collagen, Hydrolyzed Elastin, Palm Acid, Sodium Chloride, Palm Kernel Acid, Tetrasodium Etidronate(HEDP), Tetrasodium EDTA,
Fragrance, Linalool, Limonene

Other information

Protect this product from excessive heat and direct sun. Store at 40-90℉(4-35℃)